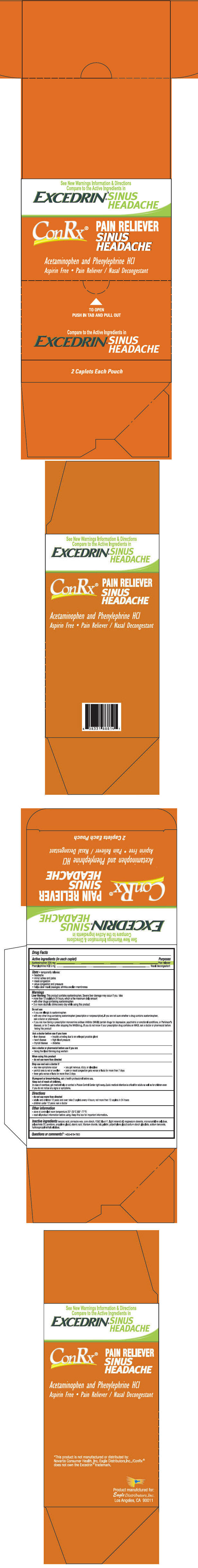 DRUG LABEL: ConRX Pain Reliever Sinus Headache
NDC: 68737-240 | Form: TABLET
Manufacturer: Eagle Distributors,Inc.
Category: otc | Type: HUMAN OTC DRUG LABEL
Date: 20140207

ACTIVE INGREDIENTS: Phenylephrine Hydrochloride 5 mg/1 1; Acetaminophen 325 mg/1 1
INACTIVE INGREDIENTS: Benzoic Acid; Carnauba Wax; Starch, Corn; Fd&C Blue No. 1; Sodium Benzoate; light mineral oil; Magnesium Stearate; Cellulose, Microcrystalline; Polysorbate 20; Povidones; Propylene Glycol; Polyethylene Glycols; Stearic acid; Titanium dioxide; Talc; Gelatin; Sodium Starch Glycolate Type A Corn; Hypromelloses

ConRX® Pain Reliever Sinus Headache

Drug Facts

ACTIVE INGREDIENT

PURPOSE

Active ingredients (in each caplet) | Purposes
Acetaminophen 325 mg | Pain reliever
Phenylephrine HCl 5 mg | Nasal decongestant

Uses

- temporarily relieves:
  - headache
  - minor aches and pains
  - nasal congestion
  - sinus congestion and pressure
  - helps clear nasal passages; shrinks swollen membranes

Warnings

Liver Warning

This product contains acetaminophen. Severe liver damage may occur if you take

- more than 12 caplets in 24 hours, which is the maximum daily amount
- with other drugs containing acetaminophen
- 3 or more alcoholic drinks every day while using this product

Do not use

- if you are allergic to acetaminophen
- with any other drug containing acetaminophen (prescription or nonprescription). If you are not sure whether a drug contains acetaminophen, ask a doctor or pharmacist.
- if you are now taking a prescription monoamine oxidase inhibitor (MAOI) (certain drugs for depression, psychiatric or emotional conditions, or Parkinson's disease), or for 2 weeks after stopping the MAOI drug. If you do not know if your prescription drug contains an MAOI, ask a doctor or pharmacist before taking this product

Ask a doctor before use if you have

- liver disease
- heart disease
- thyroid disease

- trouble urinating due to an enlarged prostate gland
- high blood pressure
- diabetes

Ask a doctor or pharmacist before use if you are

- taking the blood thinning drug warfarin

When using this product

- do not use more than directed

Stop use and ask a doctor if

- any new symptoms occur
- you get nervous, dizzy, or sleepless
- painful area is red or swollen
- pain or nasal congestion gets worse or lasts for more than 7 days
- fever gets worse or lasts for more than 3 days

PREGNANCY OR BREAST FEEDING

If pregnant or breast-feeding, ask a health professional before use.

Keep out of reach of children.

In case of overdose, get medical help or contact a Poison Control Center right away. Quick medical attention is critical for adults as well as for children even if you do not notice any signs or symptoms.

Directions

- do not use more than directed
- adults and children 12 years and over: take 2 caplets every 4 hours; not more than 12 caplets in 24 hours
- children under 12 years: ask a doctor

Other information

- store at controlled room temperature 20°-25°C (68°-77°F)
- read all product information before using. Keep this box for important information.

Inactive ingredients

benzoic acid, carnauba wax, corn starch, FD&C blue # 1, light mineral oil, magnesium stearate, microcrystalline cellulose, polysorbate 20, povidone, propylene glycol, stearic acid, titanium dioxide, talc,gelatin, polyethylene glycol sodium starch glycolate, sodium benzoate, hydroxypropylmethyl cellulose

Questions or comments?

1-855-619-7900

PRINCIPAL DISPLAY PANEL - 50 x 2 Caplet Pouch Box

See New Warnings Information & Directions
Compare to the Active Ingredients in
EXCEDRIN*® SINUS
HEADACHE

ConRx®

PAIN RELIEVER
SINUS
HEADACHE

Acetaminophen and Phenylephrine HCl

Aspirin Free • Pain Reliever / Nasal Decongestant

TO OPEN
PUSH IN TAB AND PULL OUT

Compare to the Active Ingredients in
EXCEDRIN® SINUS
HEADACHE

2 Caplets Each Pouch